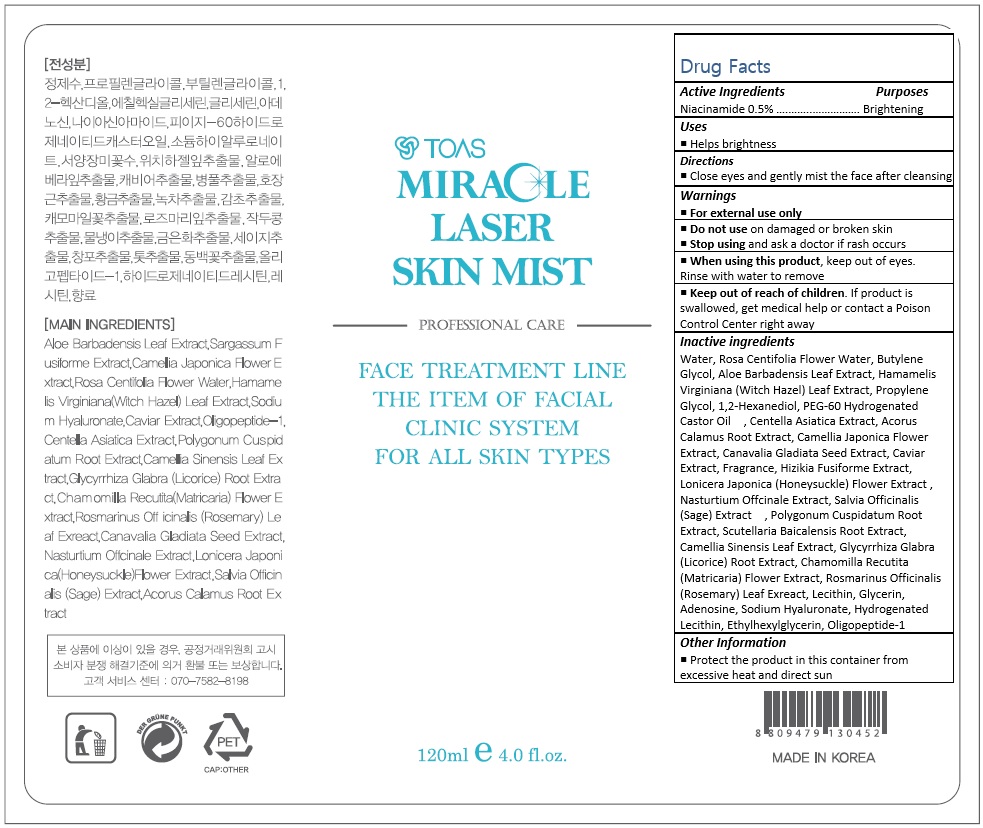 DRUG LABEL: Miracle Laser Skin Mist
NDC: 72557-003 | Form: LIQUID
Manufacturer: TOAS Co., Ltd.
Category: otc | Type: HUMAN OTC DRUG LABEL
Date: 20180924

ACTIVE INGREDIENTS: NIACINAMIDE 0.6 mg/120 mL
INACTIVE INGREDIENTS: WATER; BUTYLENE GLYCOL; ALOE VERA LEAF; HAMAMELIS VIRGINIANA LEAF; PROPYLENE GLYCOL; 1,2-HEXANEDIOL; PEG-60 HYDROGENATED CASTOR OIL; CENTELLA ASIATICA; ROSA CENTIFOLIA FLOWER; ACORUS CALAMUS ROOT; CAMELLIA JAPONICA FLOWER

72557-003_Miracle Laser Skin Mist

ACTIVE INGREDIENT

Niacinamide 0.5%

PURPOSE

Brightening

INDICATIONS AND USAGE

Helps brightness

DOSAGE AND ADMINISTRATION

Close eyes and gently mist the face after cleansing

WARNINGS

For external use only.
Do not use on damaged or broken skin.
When using this product, keep out of eyes. Rinse with water to remove.
Stop using and ask a doctor if rash occurs.

KEEP OUT OF REACH OF CHILDREN

Keep out of reach of the children. If product is swallowed, get medical help or contact a poison control center right away.

INACTIVE INGREDIENT

Water, Rosa Centifolia Flower Water, Butylene Glycol, Aloe Barbadensis Leaf Extract, Hamamelis Virginiana (Witch Hazel) Leaf Extract, Propylene Glycol, 1,2-Hexanediol, PEG-60 Hydrogenated Castor Oil , Centella Asiatica Extract, Acorus Calamus Root Extract, Camellia Japonica Flower Extract, Canavalia Gladiata Seed Extract, Caviar Extract, Fragrance, Hizikia Fusiforme Extract, Lonicera Japonica (Honeysuckle) Flower Extract , Nasturtium Offcinale Extract, Salvia Officinalis (Sage) Extract , Polygonum Cuspidatum Root Extract, Scutellaria Baicalensis Root Extract, Camellia Sinensis Leaf Extract, Glycyrrhiza Glabra (Licorice) Root Extract, Chamomilla Recutita (Matricaria) Flower Extract, Rosmarinus Officinalis (Rosemary) Leaf Exreact, Lecithin, Glycerin, Adenosine, Sodium Hyaluronate, Hydrogenated Lecithin, Ethylhexylglycerin, Oligopeptide-1